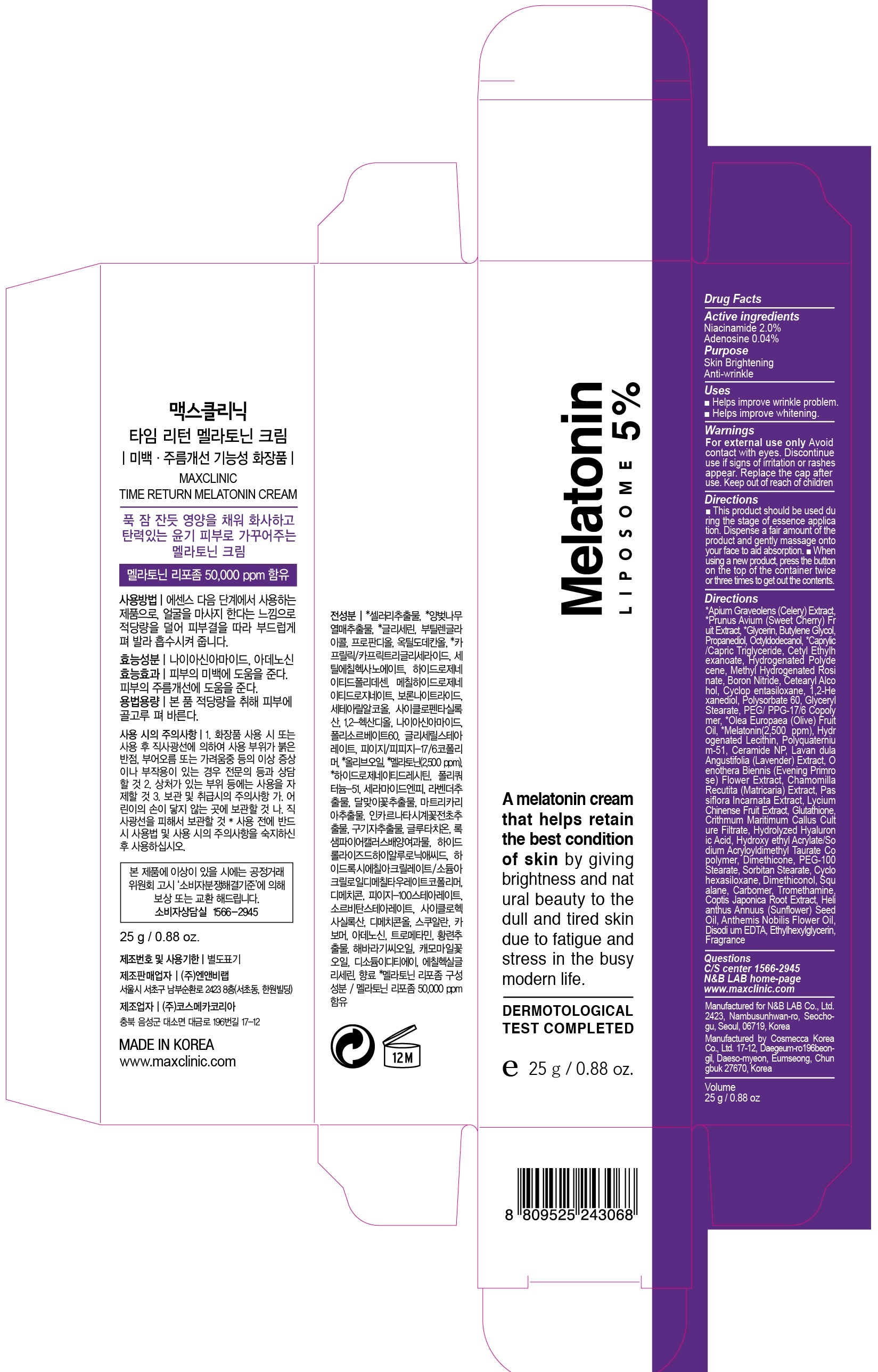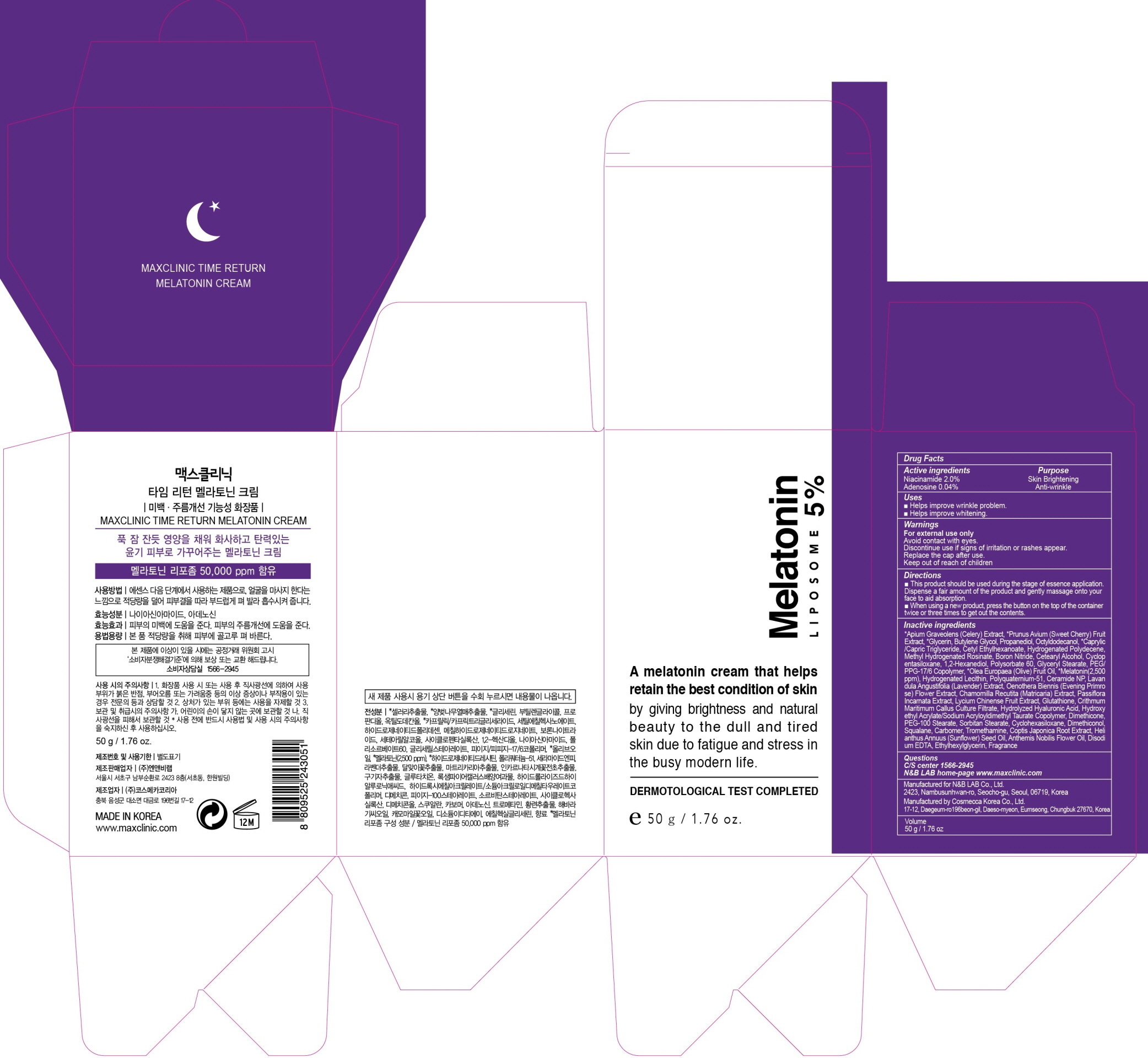 DRUG LABEL: TIME RETURN MELATONIN
NDC: 69058-610 | Form: PATCH
Manufacturer: N&B LAB.Co.Ltd
Category: otc | Type: HUMAN OTC DRUG LABEL
Date: 20181101

ACTIVE INGREDIENTS: Niacinamide 2.0 g/100 g; Adenosine 0.04 g/100 g
INACTIVE INGREDIENTS: Glycerin; Butylene Glycol

ACTIVE INGREDIENT

Active ingredients: Niacinamide 2.0%, Adenosine 0.04%

INACTIVE INGREDIENT

Inactive ingredients:

*Apium Graveolens (Celery) Extract, *Prunus Avium (Sweet Cherry) Fruit Extract, *Glycerin, Butylene Glycol, Propanediol, Octyldodecanol, *Caprylic/Capric Triglyceride, Cetyl Ethylhexanoate, Hydrogenated Polydecene, Methyl Hydrogenated Rosinate, Boron Nitride, Cetearyl Alcohol, Cyclopentasiloxane, 1,2-Hexanediol, Polysorbate 60, Glyceryl Stearate, PEG/PPG-17/6 Copolymer, *Olea Europaea (Olive) Fruit Oil, *Melatonin(2,500 ppm), Hydrogenated Lecithin, Polyquaternium-51, Ceramide NP, Lavandula Angustifolia (Lavender) Extract, Oenothera Biennis (Evening Primrose) Flower Extract, Chamomilla Recutita (Matricaria) Extract, Passiflora Incarnata Extract, Lycium Chinense Fruit Extract, Glutathione, Crithmum Maritimum Callus Culture Filtrate, Hydrolyzed Hyaluronic Acid, Hydroxyethyl Acrylate/Sodium Acryloyldimethyl Taurate Copolymer, Dimethicone, PEG-100 Stearate, Sorbitan Stearate, Cyclohexasiloxane, Dimethiconol, Squalane, Carbomer, Tromethamine, Coptis Japonica Root Extract, Helianthus Annuus (Sunflower) Seed Oil, Anthemis Nobilis Flower Oil, Disodium EDTA, Ethylhexylglycerin, Fragrance

PURPOSE

Purpose: Skin Brightening, Anti-wrinkle

WARNINGS

For external use only

Avoid contact with eyes.

Discontinue use if signs of irritation or rashes appear.

Replace the cap after use.

Keep out of reach of children

KEEP OUT OF REACH OF CHILDREN

Uses

■ Helps improve wrinkle problem.

■ Helps improve whitening.

Directions

■ This product should be used during the stage of essence application.
Dispense a fair amount of the product and gently massage onto your face to aid absorption.

■ When using a new product, press the button on the top of the container twice or three times to get out the contents.